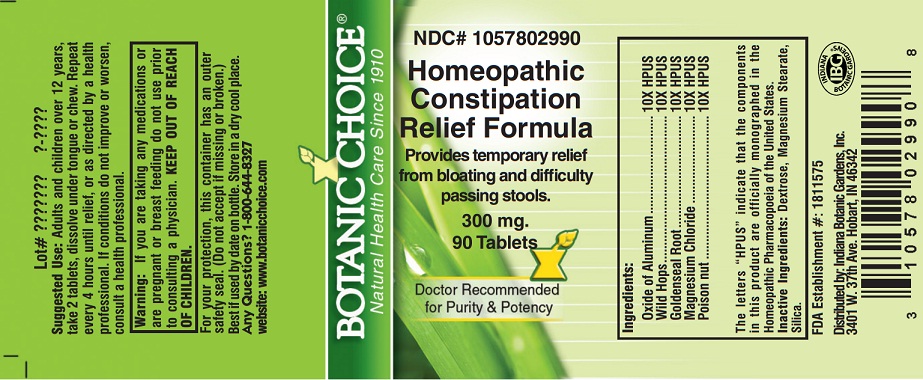 DRUG LABEL: Homeopathic Constipation Relief
NDC: 10578-029 | Form: TABLET
Manufacturer: Indiana Botanic Gardens
Category: homeopathic | Type: HUMAN OTC DRUG LABEL
Date: 20130401

ACTIVE INGREDIENTS: ALUMINUM OXIDE 10 [hp_X]/1 1; BRYONIA ALBA ROOT 10 [hp_X]/1 1; GOLDENSEAL 10 [hp_X]/1 1; MAGNESIUM CHLORIDE 10 [hp_X]/1 1; STRYCHNOS NUX-VOMICA SEED 10 [hp_X]/1 1
INACTIVE INGREDIENTS: DEXTROSE; MAGNESIUM STEARATE; SILICON DIOXIDE

Homeopathic Constipation Relief

Suggested Use:

Adults and children over 12 years, take 2 tablets, dissolve under tongue or chew. Repeat every 4 hours until relief, or as directed by a health professional.

STOP USE

If conditions do not improve or worsen, consult a health professional.

Warning:

If you are taking any medications or are pregnant or breast feeding do not use prior to consulting a physician.

KEEP OUT OF REACH OF CHILDREN.

For your protection, this container has an outer safety seal. (Do not accept if missing or broken.) Best if used by date on bottle. Store in a dry cool place.

Any Questions?

Any Questions? 1-800-644-8327

website: www.botanicchoice.com

PURPOSE

INDICATIONS AND USAGE

Provides temporary relief from bloating and difficulty passing stools.

Ingredients:

Oxide of Aluminum ............................10X HPUS

Wild Hops ..........................................10X HPUS

Goldenseal Root ................................10X HPUS

Magnesium Chloride .........................10X HPUS

Poison nut .........................................10X HPUS

The letters “HPUS” indicate that the components in this product are officially monographed in the Homeopathic Pharmacopoeia of the United States.

Inactive Ingredients:

Dextrose, Magnesium Stearate, Silica.

FDA Establishment #: 1811575

Distributed by: Indiana Botanic Gardens, Inc.

3401 W. 37th Ave. Hobart, IN 46342

Botanic Choice®

Natural Health Care Since 1910

NDC# 1057802990

Homeopathic Constipation Relief Formula

Provides temporary relief from bloating and difficulty passing stools.

300 mg.

90 Tablets

Doctor Recommended for Purity & Potency